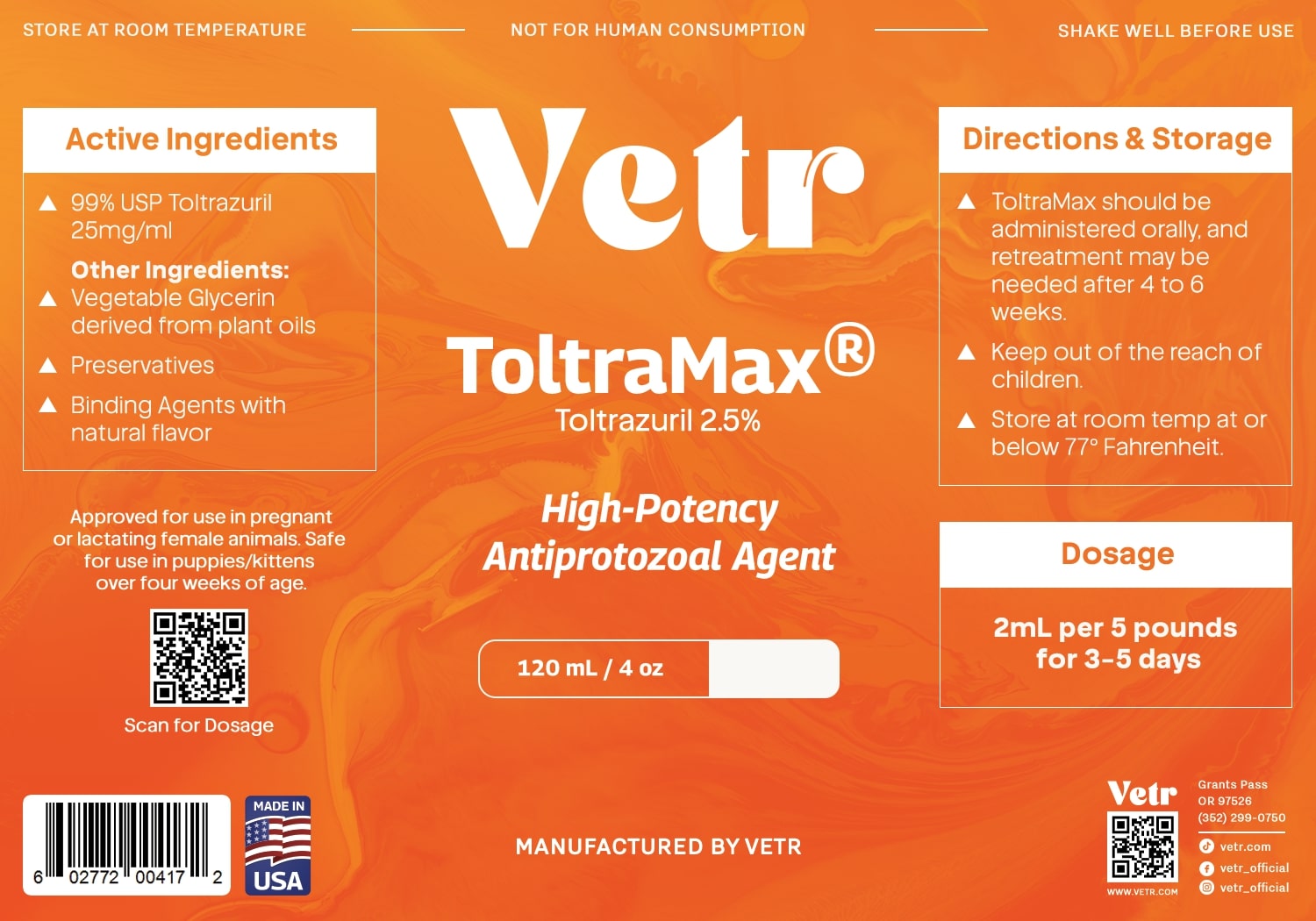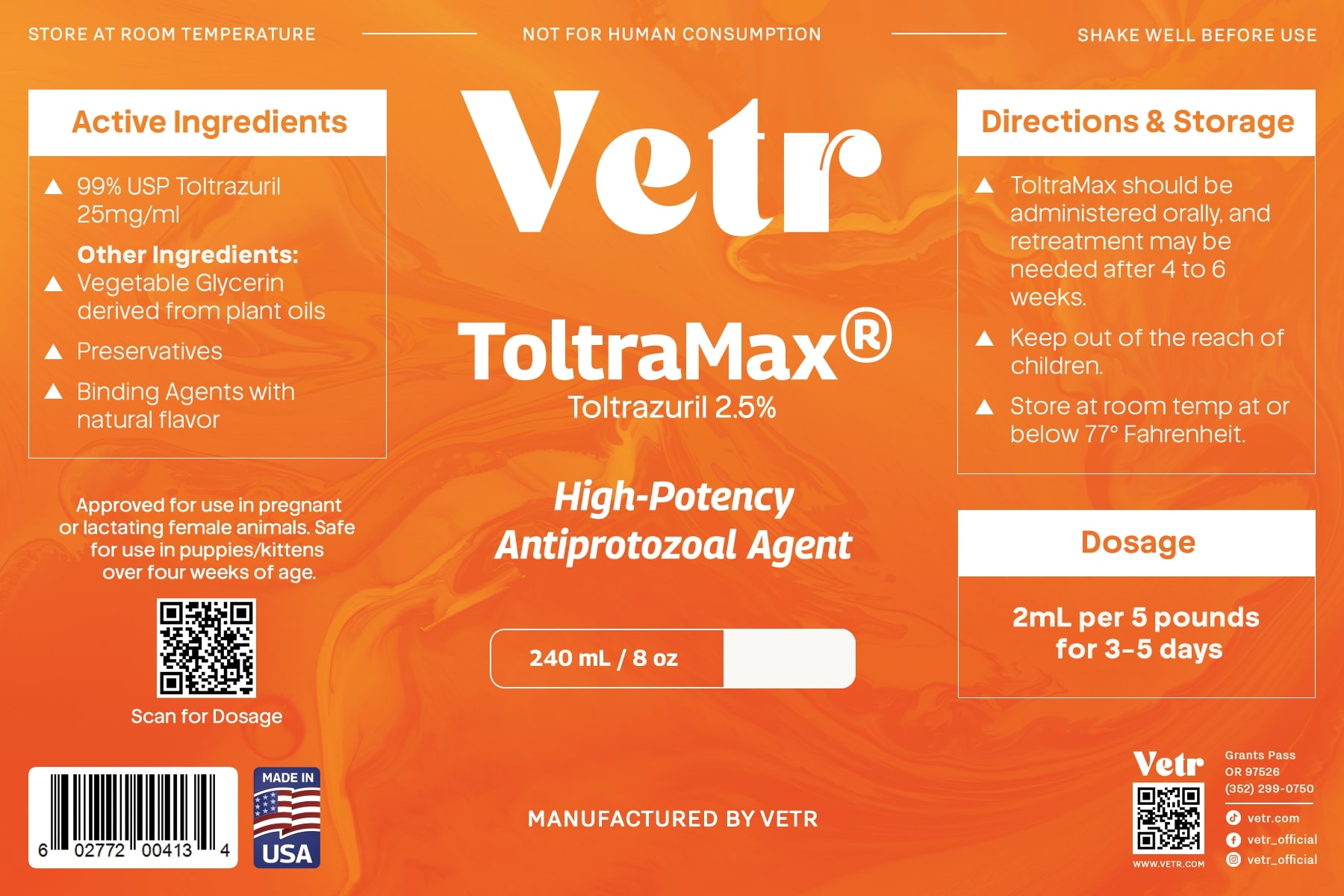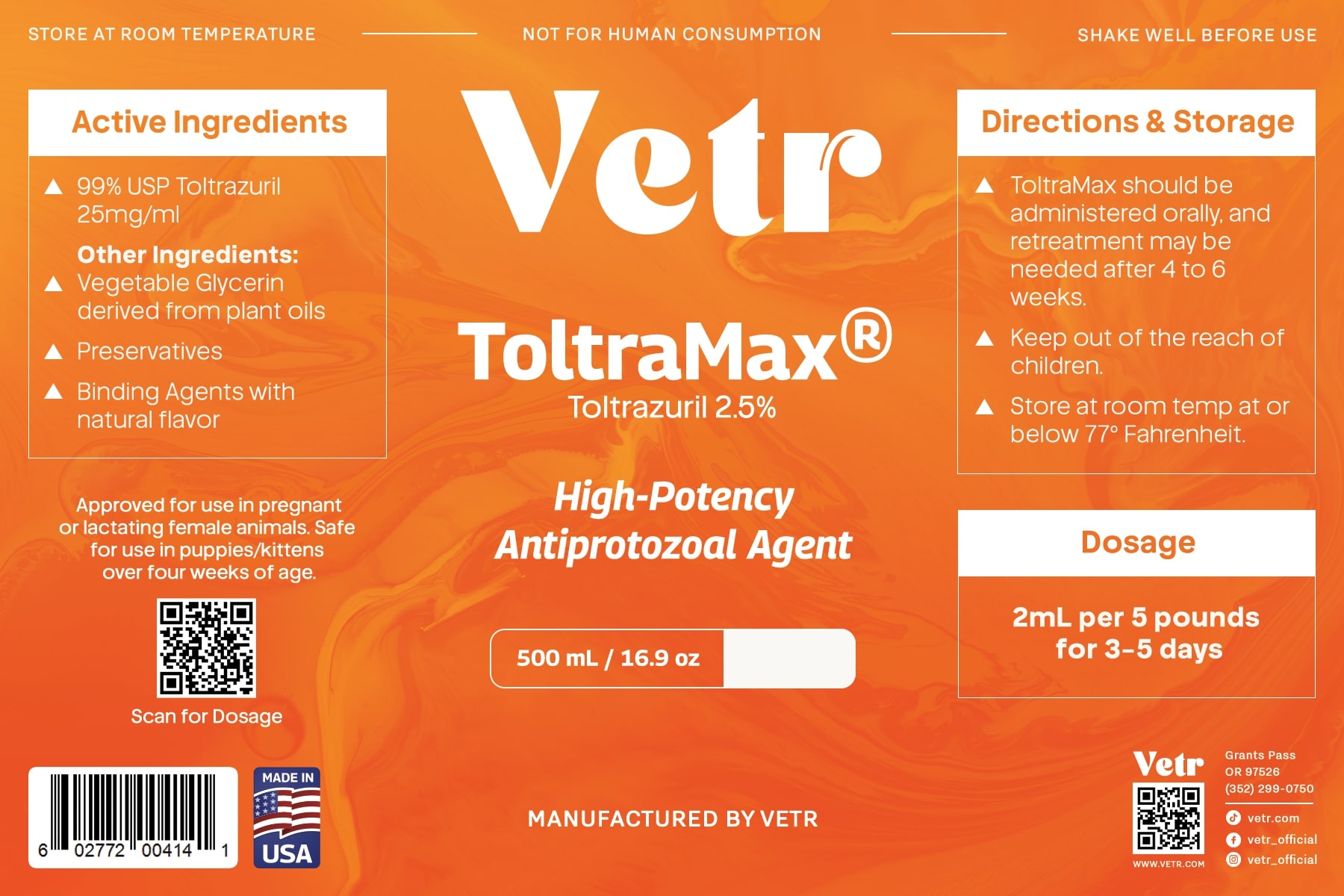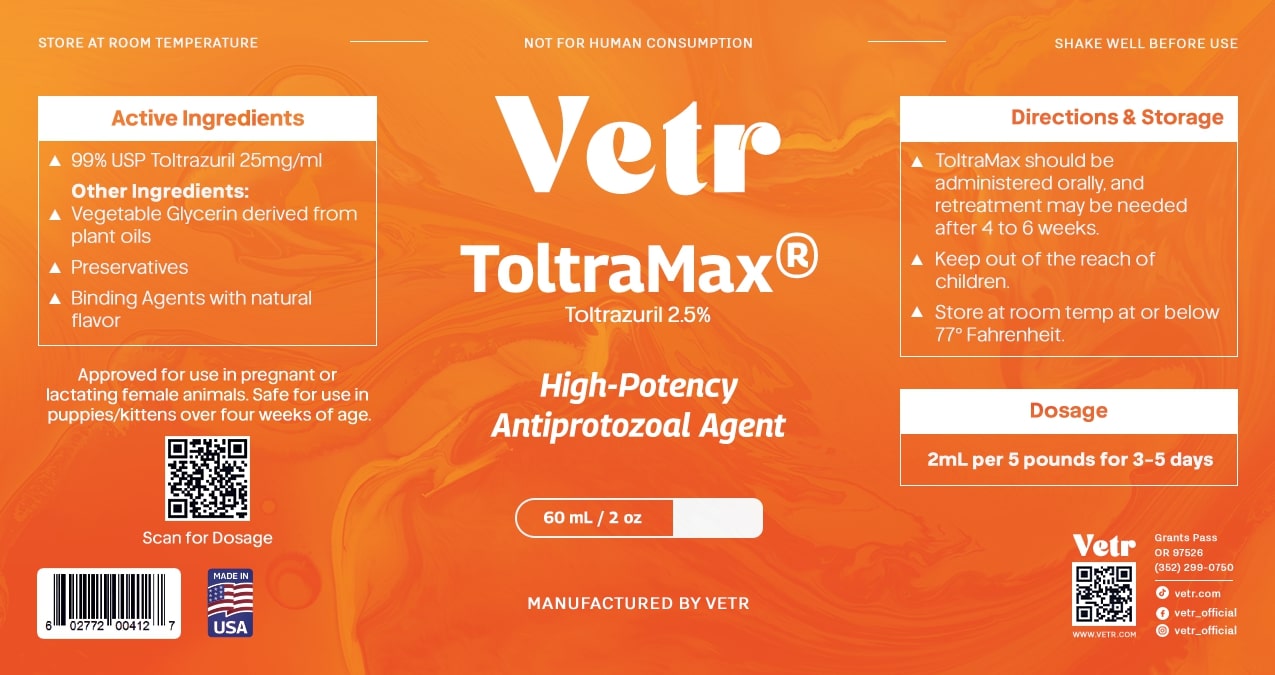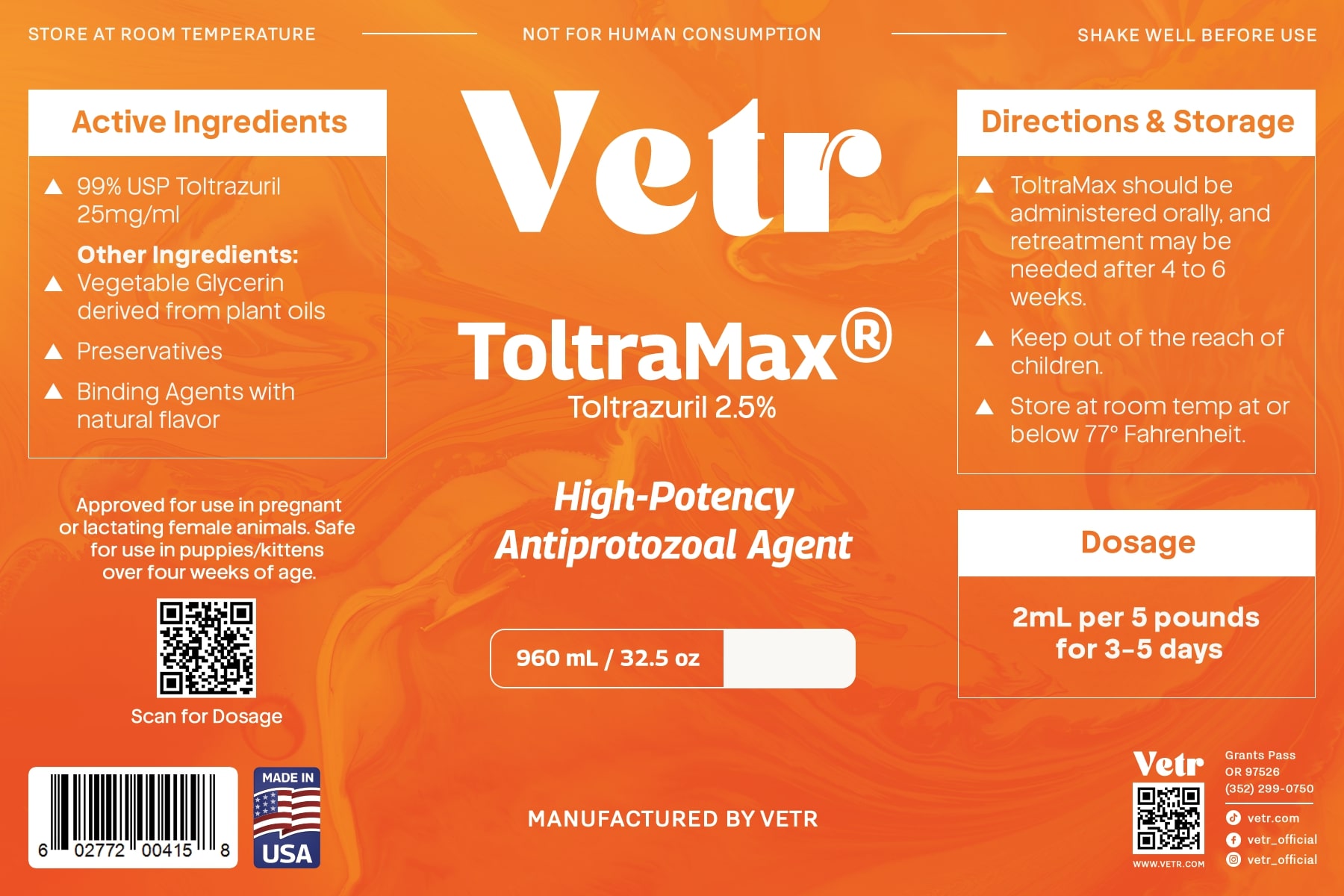 DRUG LABEL: Toltramax 2.5% suspension
NDC: 86213-122 | Form: LIQUID
Manufacturer: Vetr, LLC
Category: animal | Type: OTC ANIMAL DRUG LABEL
Date: 20251214

ACTIVE INGREDIENTS: TOLTRAZURIL 25 mg/1 mL
INACTIVE INGREDIENTS: WATER; GLYCERIN; PROPYLPARABEN; METHYLPARABEN

Toltramax 2.5% (2.5% toltrazuril suspension)

Keep out of reach of children. Recognized as safe for use in pregnant and lactating females and puppies & kittens over four weeks of age.

DOSAGE AND ADMINISTRATION

Shake well before use. Dose at 2 mL (50 mg toltrazuril) per 5 pounds of body weight, for 3-5 consecutive days. Toltramax should be administered orally and retreatment may be necessary after 4-6 weeks.

STORAGE AND HANDLING

Store at room temperature (at or below 77F). Do not allow to freeze.

ACTIVE INGREDIENT

Toltrazuril USP, 2.5% suspension (25 mg/mL)

INACTIVE INGREDIENT

Glycerin USP, methyl- and propylparaben (preservative), purified water.